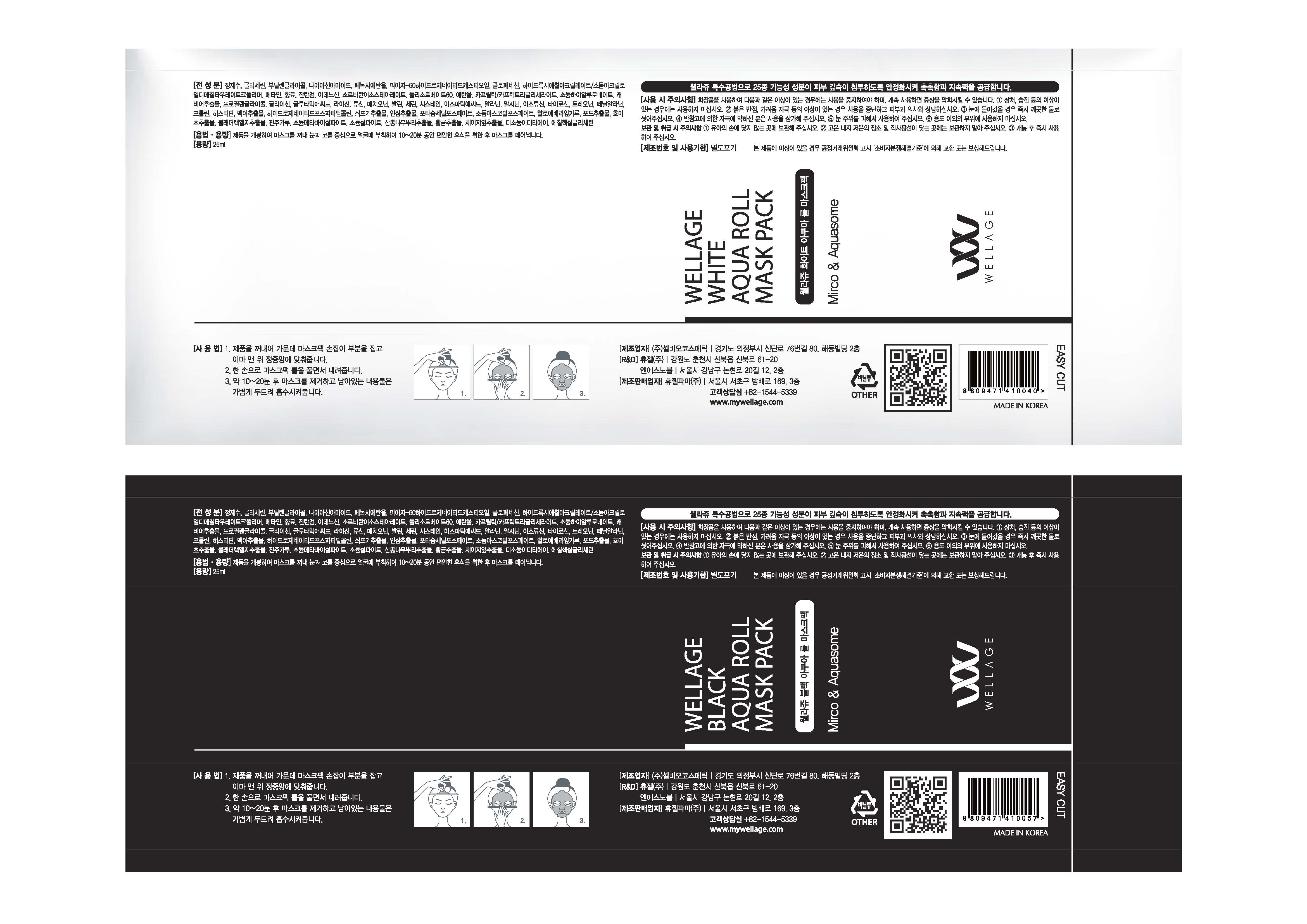 DRUG LABEL: WELLAGE WHITE AQUA ROLL MASK PACK
NDC: 69346-0004 | Form: PATCH
Manufacturer: HUGEL PHARMA CO.,LTD
Category: otc | Type: HUMAN OTC DRUG LABEL
Date: 20160907

ACTIVE INGREDIENTS: GLYCERIN 10 g/100 mL
INACTIVE INGREDIENTS: WATER; BUTYLENE GLYCOL; NIACINAMIDE; ADENOSINE

Drug Facts

ACTIVE INGREDIENT

glycerin

INACTIVE INGREDIENT

water, butylene glycol, adenosine, niacinamide, etc.

PURPOSE

Skin protectant

keep out of reach of the children

INDICATIONS AND USAGE

1. Remove mask. Hold the rod horizontally and align it to the center of the forehead.
2. Use free hand to unravel the mask sheet from the rod and position mask on face.
3. Peel off mask in 10-20 minutes and pat in remaining essence to absorb into skin.

WARNINGS

1. Do not use in the following cases(Eczema and scalp wounds)

2.Side Effects

1)Due to the use of this product, if rash, irritation, itching and symptopms of hypersnesitivity occur dicontinue use and consult your pharmacist or doctor

3.General Precautions

1)If in contact with the eyes, wash out thoroughty with water If the symptoms are servere, seek medical advice immediately

2)This product is for exeternal use only. Do not use for internal use

4.Storage and handling precautions

1)If possible, avoid direct sunlight and store in cool and area of low humidity

2)In order to maintain the quality of the product and avoid misuse

3)Avoid placing the product near fire and store out in reach of children

DOSAGE AND ADMINISTRATION

for external use only